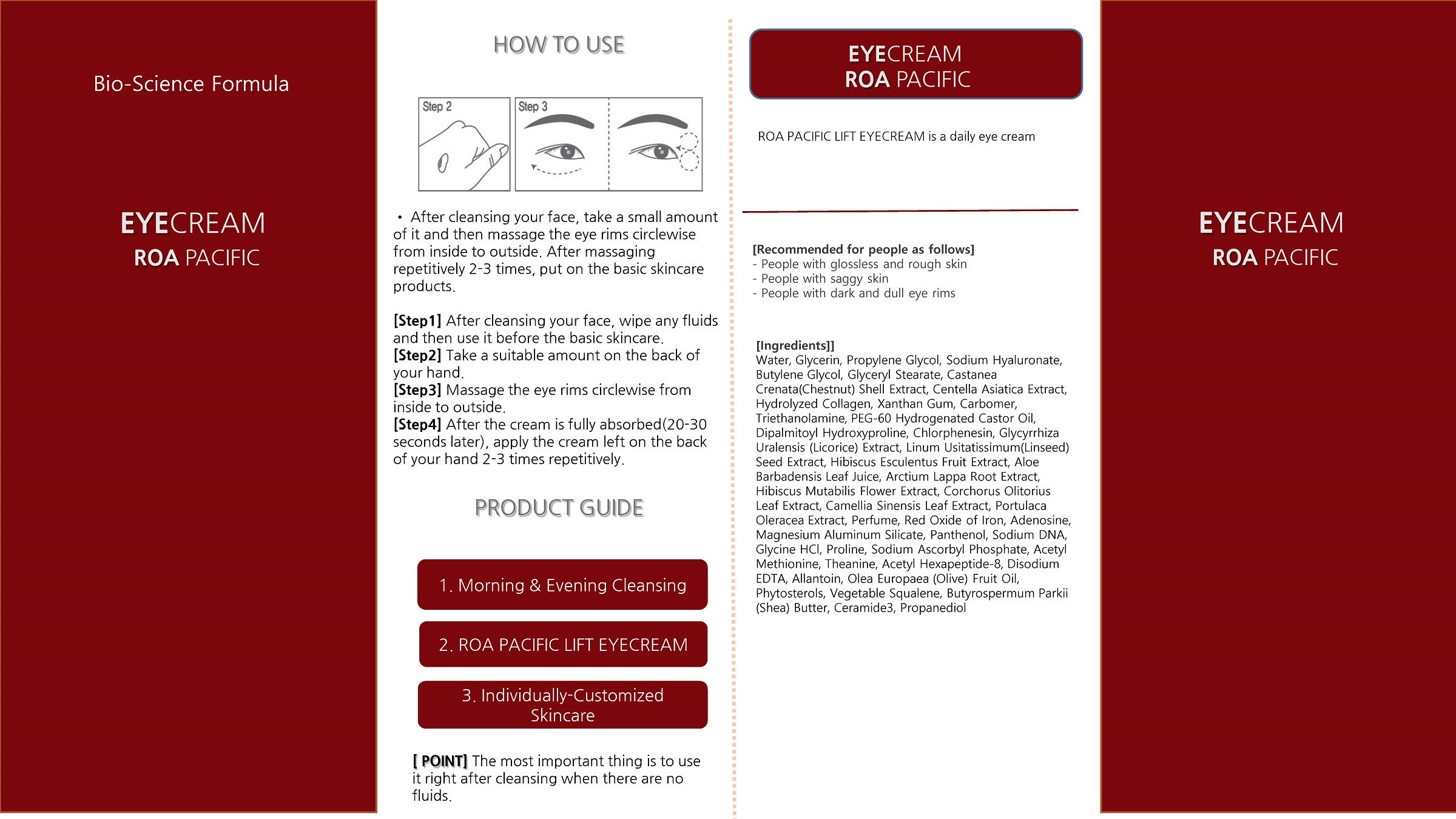 DRUG LABEL: LIFT EYECREAM
NDC: 73490-0001 | Form: CREAM
Manufacturer: ROA Pacific Corporation
Category: otc | Type: HUMAN OTC DRUG LABEL
Date: 20221031

ACTIVE INGREDIENTS: GLYCERIN 5 g/100 mL
INACTIVE INGREDIENTS: WATER; BUTYLENE GLYCOL

Drug Facts

ACTIVE INGREDIENT

glycerin

INACTIVE INGREDIENT

Water, Propylene Glycol, Sodium Hyaluronate, Butylene Glycol, Glyceryl Stearate, Castanea Crenata(Chestnut) Shell Extract, Centella Asiatica Extract, Hydrolyzed Collagen, Xanthan Gum, Carbomer, Triethanolamine, PEG-60 Hydrogenated Castor Oil, Dipalmitoyl Hydroxyproline, Chlorphenesin, Glycyrrhiza Uralensis (Licorice) Extract, Linum Usitatissimum(Linseed) Seed Extract, Hibiscus Esculentus Fruit Extract, Aloe Barbadensis Leaf Juice, Arctium Lappa Root Extract, Hibiscus Mutabilis Flower Extract, Corchorus Olitorius Leaf Extract, Camellia Sinensis Leaf Extract, Portulaca Oleracea Extract, Perfume, Red Oxide of Iron, Adenosine, Magnesium Aluminum Silicate, Panthenol, Sodium DNA, Glycine HCl, Proline, Sodium Ascorbyl Phosphate, Acetyl Methionine, Theanine, Acetyl Hexapeptide-8, Disodium EDTA, Allantoin, Olea Europaea (Olive) Fruit Oil, Phytosterols, Vegetable Squalene, Butyrospermum Parkii (Shea) Butter, Ceramide3, Propanediol

PURPOSE

-The instant botox effect lasts average 5-8hours just like a magic of two minutes.

-Great effects on skin moisturizing and pore tightening

-Overall lifting effect when it is applied to the whole face

-Non-sticky and smooth texture

keep out of reach of the children

INDICATIONS AND USAGE

• After cleansing your face, take a small amount of it and then massage the eye rims circlewise from inside to outside. After massaging repetitively 2-3 times, put on the basic skincare products.

[Step1] After cleansing your face, wipe any fluids and then use it before the basic skincare.

[Step2] Take a suitable amount on the back of your hand.

[Step3] Massage the eye rims circlewise from inside to outside.

[Step4] After the cream is fully absorbed(20-30 seconds later), apply the cream left on the back of your hand 2-3 times repetitively.

WARNINGS

■ if following abnormal symptoms occurs after use , stop use and consult with a skin specialist

red specks, swelling, itching

■ don’t use on the part where there is injury, eczema, or dermatitis

Keep out of reach of children

■ if swallowed, get medical help or contact a person control center immediately

DOSAGE AND ADMINISTRATION

for external use only